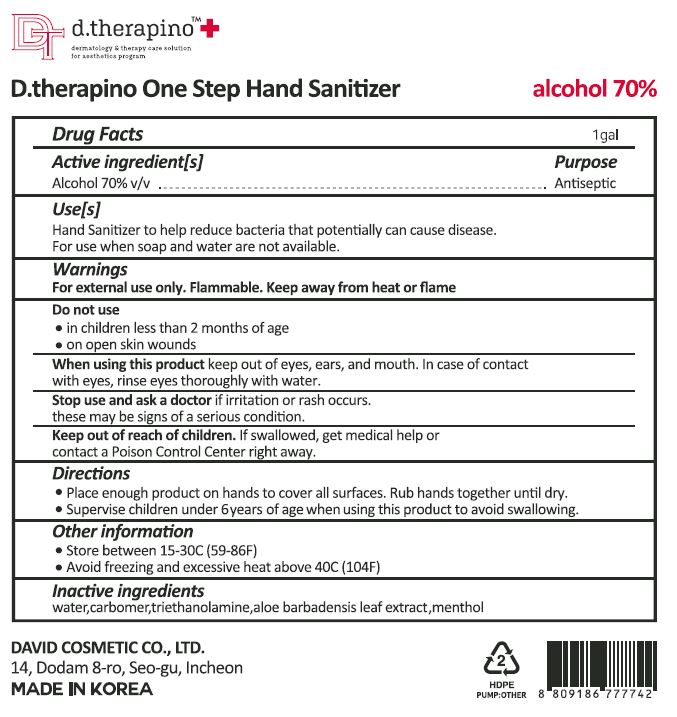 DRUG LABEL: d.therapino One Step Hand Sanitizer
NDC: 58241-0008 | Form: GEL
Manufacturer: David Cosmetic Co Ltd
Category: otc | Type: HUMAN OTC DRUG LABEL
Date: 20200612

ACTIVE INGREDIENTS: ALCOHOL 70 g/100 mL
INACTIVE INGREDIENTS: MENTHOL; CARBOMER 940; TROLAMINE; WATER; ALOE VERA LEAF; 1,2-HEXANEDIOL; BUTYLENE GLYCOL

Drug Facts

ACTIVE INGREDIENT

alcohol

INACTIVE INGREDIENT

water, aloe extract, carbomer, menthol, triethanolamine, butylene glycol, 1,2-hexanediol

KEEP OUT OF REACH OF THE CHILDREN

PURPOSE

hand sanitizer to help reduce bacteria that potentially can cause disease

for use when soap and water are not available

INDICATIONS AND USAGE

hand sanitizer to help reduce bacteria that potentially can cause disease

for use when soap and water are not available

WARNINGS

For external use only.

Flammable, keep away from fire or flame.

When using this product keep out of eyes. If contact with eyes occurs, rinse promptly and thoroughly with water.

Stop use and ask a doctor if significant irritation or sensitization develops.

Keep out of reach of children. If swallowed, get medical help or contact a Poison Control Center right away.

DOSAGE AND ADMINISTRATION

for external use only